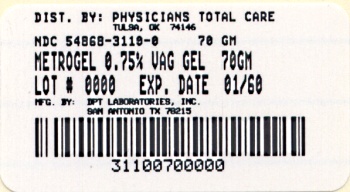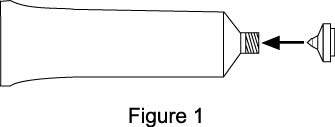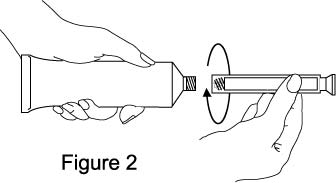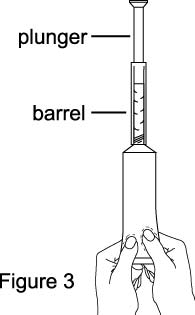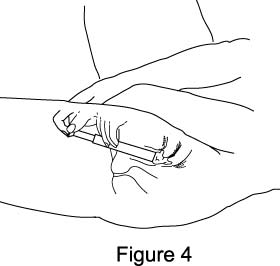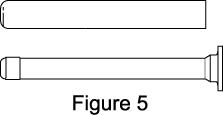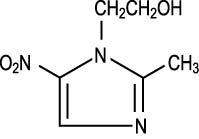 DRUG LABEL: METROGEL
NDC: 54868-3110 | Form: GEL
Manufacturer: Physicians Total Care, Inc.
Category: prescription | Type: HUMAN PRESCRIPTION DRUG LABEL
Date: 20110331

ACTIVE INGREDIENTS: METRONIDAZOLE 7.5 mg/1 g
INACTIVE INGREDIENTS: CARBOMER 934; EDETATE DISODIUM; METHYLPARABEN; SODIUM HYDROXIDE; PROPYLENE GLYCOL; PROPYLPARABEN

FOR INTRAVAGINAL USE ONLY

NOT FOR OPHTHALMIC, DERMAL, OR ORAL USE

DESCRIPTION

METROGEL-VAGINAL is the intravaginal dosage form of the synthetic antibacterial agent, metronidazole, USP at a concentration of 0.75%. Metronidazole is a member of the imidazole class of antibacterial agents and is classified therapeutically as an antiprotozoal and antibacterial agent. Chemically, metronidazole is a 2-methyl-5-nitroimidazole-1-ethanol. It has a chemical formula of C6H9N3O3, a molecular weight of 171.16, and has the following structure:

METROGEL-VAGINAL is a gelled, purified water solution, containing metronidazole at a concentration of 7.5 mg/g (0.75%). The gel is formulated at pH 4.0. The gel also contains carbomer 934P, edetate disodium, methyl paraben, propyl paraben, propylene glycol, and sodium hydroxide.

Each applicator full of 5 grams of vaginal gel contains approximately 37.5 mg of metronidazole.

CLINICAL PHARMACOLOGY

Normal Subjects:

Following a single, intravaginal 5 gram dose of metronidazole vaginal gel (equivalent to 37.5 mg of metronidazole) to 12 normal subjects, a mean maximum serum metronidazole concentration of 237 ng/mL was reported (range: 152 to 368 ng/mL). This is approximately 2% of the mean maximum serum metronidazole concentration reported in the same subjects administered a single, oral 500 mg dose of metronidazole (mean Cmax = 12,785 ng/mL, range: 10,013 to 17,400 ng/mL). These peak concentrations were obtained in 6 to 12 hours after dosing with metronidazole vaginal gel and 1 to 3 hours after dosing with oral metronidazole.

The extent of exposure [area under the curve (AUC)] of metronidazole, when administered as a single intravaginal 5 gram dose of metronidazole vaginal gel (equivalent to 37.5 mg of metronidazole), was approximately 4% of the AUC of a single oral 500 mg dose of metronidazole (4977 ng-hr/mL and approximately 125,000 ng-hr/mL, respectively).

Dose-adjusted comparisons of AUCs demonstrated that, on a mg to mg comparison basis, the absorption of metronidazole, when administered vaginally, was approximately half that of an equivalent oral dosage.

Patients with Bacterial Vaginosis:

Following single and multiple 5 gram doses of metronidazole vaginal gel to 4 patients with bacterial vaginosis, a mean maximum serum metronidazole concentration of 214 ng/mL on day 1 and 294 ng/mL (range: 228 to 349 ng/mL) on day five were reported. Steady state metronidazole serum concentrations following oral dosages of 400 to 500 mg BID have been reported to range from 6,000 to 20,000 ng/mL.

Microbiology:

The intracellular targets of action of metronidazole on anaerobes are largely unknown. The 5-nitro group of metronidazole is reduced by metabolically active anaerobes, and studies have demonstrated that the reduced form of the drug interacts with bacterial DNA. However, it is not clear whether interaction with DNA alone is an important component in the bactericidal action of metronidazole on anaerobic organisms.

Culture and sensitivity testing of bacteria are not routinely performed to establish the diagnosis of bacterial vaginosis. (See INDICATIONS AND USAGE.)

Standard methodology for the susceptibility testing of the potential bacterial vaginosis pathogens, Gardnerella vaginalis, Mobiluncus spp., and Mycoplasma hominis, has not been defined. Nonetheless, metronidazole is an antimicrobial agent active in vitro against most strains of the following organisms that have been reported to be associated with bacterial vaginosis:

Bacteroides spp.
Gardnerella vaginalis
Mobiluncus spp.
Peptostreptococcus spp.

INDICATIONS AND USAGE

METROGEL-VAGINAL is indicated in the treatment of bacterial vaginosis (formerly referred to as Haemophilus vaginitis, Gardnerella vaginitis, nonspecific vaginitis, Corynebacterium vaginitis, or anaerobic vaginosis).

NOTE: For purposes of this indication, a clinical diagnosis of bacterial vaginosis is usually defined by the presence of a homogeneous vaginal discharge that (a) has a pH of greater than 4.5, (b) emits a “fishy” amine odor when mixed with a 10% KOH solution, and (c) contains clue cells on microscopic examination. Gram’s stain results consistent with a diagnosis of bacterial vaginosis include (a) markedly reduced or absent Lactobacillus morphology, (b) predominance of Gardnerella morphotype, and (c) absent or few white blood cells.

Other pathogens commonly associated with vulvovaginitis, e.g., Trichomonas vaginalis, Chlamydia trachomatis, N. gonorrhoeae, Candida albicans, and Herpes simplex virus should be ruled out.

CONTRAINDICATIONS

METROGEL-VAGINAL is contraindicated in patients with a prior history of hypersensitivity to metronidazole, parabens, other ingredients of the formulation, or other nitroimidazole derivatives.

WARNINGS

Convulsive Seizures and Peripheral Neuropathy:

Convulsive seizures and peripheral neuropathy, the latter characterized mainly by numbness or paresthesia of an extremity, have been reported in patients treated with oral or intravenous metronidazole. The appearance of abnormal neurologic signs demands the prompt discontinuation of metronidazole vaginal gel therapy. Metronidazole vaginal gel should be administered with caution to patients with central nervous system diseases.

Psychotic Reactions:

Psychotic reactions have been reported in alcoholic patients who were using oral metronidazole and disulfiram concurrently. Metronidazole vaginal gel should not be administered to patients who have taken disulfiram within the last two weeks.

PRECAUTIONS

METROGEL-VAGINAL affords minimal peak serum levels and systemic exposure (AUCs) of metronidazole compared to 500 mg oral metronidazole dosing. Although these lower levels of exposure are less likely to produce the common reactions seen with oral metronidazole, the possibility of these and other reactions cannot be excluded presently. Data from well-controlled trials directly comparing metronidazole administered orally to metronidazole administered vaginally are not available.

General:

Patients with severe hepatic disease metabolize metronidazole slowly. This results in the accumulation of metronidazole and its metabolites in the plasma. Accordingly, for such patients, metronidazole vaginal gel should be administered cautiously.

Known or previously unrecognized vaginal candidiasis may present more prominent symptoms during therapy with metronidazole vaginal gel. Approximately 6-10% of patients treated with METROGEL-VAGINAL developed symptomatic Candida vaginitis during or immediately after therapy.

Disulfiram-like reaction to alcohol has been reported with oral metronidazole, thus the possibility of such a reaction occurring while on metronidazole vaginal gel therapy cannot be excluded.

METROGEL-VAGINAL contains ingredients that may cause burning and irritation of the eye. In the event of accidental contact with the eye, rinse the eye with copious amounts of cool tap water.

Information for the Patient:

The patient should be cautioned about drinking alcohol while being treated with metronidazole vaginal gel. While blood levels are significantly lower with METROGEL-VAGINAL than with usual doses of oral metronidazole, a possible interaction with alcohol cannot be excluded.

The patient should be instructed not to engage in vaginal intercourse during treatment with this product.

Drug Interactions:

Oral metronidazole has been reported to potentiate the anticoagulant effect of warfarin and other coumarin anticoagulants, resulting in a prolongation of prothrombin time. This possible drug interaction should be considered when metronidazole vaginal gel is prescribed for patients on this type of anticoagulant therapy.

In patients stabilized on relatively high doses of lithium, short-term oral metronidazole therapy has been associated with elevation of serum lithium levels and, in a few cases, signs of lithium toxicity.

Use of cimetidine with oral metronidazole may prolong the half-life and decrease plasma clearance of metronidazole.

Drug/Laboratory Test Interactions:

Metronidazole may interfere with certain types of determinations of serum chemistry values, such as aspartate aminotransferase (AST, SGOT), alanine aminotransferase (ALT, SGPT), lactate dehydrogenase (LDH), triglycerides, and glucose hexokinase. Values of zero may be observed. All of the assays in which interference has been reported involve enzymatic coupling of the assay to oxidation-reduction of nicotinamide-adenine dinucleotides (NAD + NADH). Interference is due to the similarity in absorbance peaks of NADH (340 nm) and metronidazole (322 nm) at pH 7.

Carcinogenesis, Mutagenesis, Impairment of Fertility:

Metronidazole has shown evidence of carcinogenic activity in a number of studies involving chronic oral administration in mice and rats. Prominent among the effects in the mouse was the promotion of pulmonary tumorigenesis. This has been observed in all six reported studies in that species, including one study in which the animals were dosed on an intermittent schedule (administration during every fourth week only). At very high dose levels (approximately 500 mg/kg/day), there was a statistically significant increase in the incidence of malignant liver tumors in males. Also, the published results of one of the mouse studies indicate an increase in the incidence of malignant lymphomas as well as pulmonary neoplasms associated with lifetime feeding of the drug. All these effects are statistically significant. Several long-term oral dosing studies in the rat have been completed. There were statistically significant increases in the incidence of various neoplasms, particularly in mammary and hepatic tumors, among female rats administered metronidazole over those noted in the concurrent female control groups. Two lifetime tumorigenicity studies in hamsters have been performed and reported to be negative.

These studies have not been conducted with 0.75% metronidazole vaginal gel, which would result in significantly lower systemic blood levels than those obtained with oral formulations.

Although metronidazole has shown mutagenic activity in a number of in vitro assay systems, studies in mammals (in vivo) have failed to demonstrate a potential for genetic damage.

Fertility studies have been performed in mice up to six times the recommended human oral dose (based on mg/m^2) and have revealed no evidence of impaired fertility.

Pregnancy: Teratogenic Effects: Pregnancy Category B

There has been no experience to date with the use of METROGEL-VAGINAL in pregnant patients. Metronidazole crosses the placental barrier and enters the fetal circulation rapidly. No fetotoxicity or teratogenicity was observed when metronidazole was administered orally to pregnant mice at six times the recommended human dose (based on mg/m^2); however, in a single small study where the drug was administered intraperitoneally, some intrauterine deaths were observed. The relationship of these findings to the drug is unknown.

There are, however, no adequate and well-controlled studies in pregnant women. Because animal reproduction studies are not always predictive of human response, and because metronidazole is a carcinogen in rodents, this drug should be used during pregnancy only if clearly needed.

Nursing Mothers:

Specific studies of metronidazole levels in human milk following intravaginally administered metronidazole have not been performed. However, metronidazole is secreted in human milk in concentrations similar to those found in plasma following oral administration of metronidazole.

Because of the potential for tumorigenicity shown for metronidazole in mouse and rat studies, a decision should be made whether to discontinue nursing or to discontinue the drug, taking into account the importance of the drug to the mother.

Pediatric Use:

Safety and effectiveness in children have not been established.

ADVERSE REACTIONS

Clinical Trials:

There were no deaths or serious adverse events related to drug therapy in clinical trials involving 800 non-pregnant women who received METROGEL-VAGINAL.

In a randomized, single-blind clinical trial of 505 non-pregnant women who received METROGEL-VAGINAL once or twice a day, 2 patients (one from each regimen) discontinued therapy early due to drug-related adverse events. One patient discontinued drug because of moderate abdominal cramping and loose stools, while the other patient discontinued drug because of mild vaginal burning. These symptoms resolved after discontinuation of drug.

Medical events judged to be related, probably related, or possibly related to administration of METROGEL-VAGINAL once or twice a day were reported for 195/505 (39%) patients. The incidence of individual adverse reactions were not significantly different between the two regimens. Unless percentages are otherwise stipulated, the incidence of individual adverse reactions listed below was less than 1%:

Reproductive:
Vaginal discharge (12%),
Symptomatic Candida cervicitis/vaginitis (10%),
Vulva/vaginal irritative symptoms (9%),
Pelvic discomfort (3%).

Gastrointestinal:
Gastrointestinal discomfort (7%),
Nausea and/or vomiting (4%),
Unusual taste (2%),
Diarrhea/loose stools (1%),
Decreased appetite (1%),
Abdominal bloating/gas; thirsty, dry mouth.

Neurologic:
Headache (5%),
Dizziness (2%),
Depression.

Dermatologic:
Generalized itching or rash.

Other:
Unspecified cramping (1%),
Fatigue,
Darkened urine.

In previous clinical trials submitted for approved labeling of METROGEL-VAGINAL the following was also reported:

Laboratory:
Increased/decreased white blood cell counts (1.7%).

Other Metronidazole Formulations:

Other effects that have been reported in association with the use of topical (dermal) formulations of metronidazole include skin irritation, transient skin erythema, and mild skin dryness and burning. None of these adverse events exceeded an incidence of 2% of patients

METROGEL-VAGINAL affords minimal peak serum levels and systemic exposure (AUC) of metronidazole compared to 500 mg oral metronidazole dosing. Although these lower levels of exposure are less likely to produce the common reactions seen with oral metronidazole, the possibility of these and other reactions cannot be excluded presently.

The following adverse reactions and altered laboratory tests have been reported with the oral or parenteral use of metronidazole:

Cardiovascular: Flattening of the T-wave may be seen in electrocardiographic tracings.
Central Nervous System: (See WARNINGS.) Headache, dizziness, syncope, ataxia, confusion, convulsive seizures, peripheral neuropathy, vertigo, incoordination, irritability, depression, weakness, insomnia.
Gastrointestinal: Abdominal discomfort, nausea, vomiting, diarrhea, an unpleasant metallic taste, anorexia, epigastric distress, abdominal cramping, constipation, “furry” tongue, glossitis, stomatitis, pancreatitis, and modification of taste of alcoholic beverages.
Genitourinary: Overgrowth of Candida in the vagina, dyspareunia, decreased libido, proctitis.
Hematopoietic: Reversible neutropenia, reversible thrombocytopenia.
Hypersensitivity Reactions: Urticaria; erythematous rash; flushing; nasal congestion; dryness of the mouth, vagina, or vulva; fever; pruritus; fleeting joint pains.
Renal: Dysuria, cystitis, polyuria, incontinence, a sense of pelvic pressure, darkened urine.

OVERDOSAGE

There is no human experience with overdosage of metronidazole vaginal gel. Vaginally applied metronidazole gel, 0.75% could be absorbed in sufficient amounts to produce systemic effects. (See WARNINGS.)

DOSAGE AND ADMINISTRATION

The recommended dose is one applicator full of METROGEL-VAGINAL (approximately 5 grams containing approximately 37.5 mg of metronidazole) intravaginally once or twice a day for 5 days. For once a day dosing, METROGEL-VAGINAL should be administered at bedtime.

HOW SUPPLIED

METROGEL-VAGINAL (metronidazole vaginal gel) 0.75% Vaginal Gel is supplied in a 70 gram tube and packaged with 5 vaginal applicators.

70 gram tube NDC 54868-3110-0.

Store at controlled room temperature 15° to 30°C (59° to 86°F). Protect from freezing.

Clinical Studies

In a randomized, single-blind clinical trial of non-pregnant women with bacterial vaginosis who received METROGEL-VAGINAL daily for 5 days, the clinical cure rates for evaluable patients determined at 4 weeks after completion of therapy for the QD and BID regimens were 98/185 (53%) and 109/190 (57%), respectively.

Rx only

Manufactured for | Manufactured by | Relabeling of "Additonal" barcode label by
Graceway Pharmaceuticals, LLC | DPT Laboratories, Inc. | Physicians Total Care, Inc.
Bristol, TN 37620 | San Antonio, TX 78215 | Tulsa, OK 74146

July 2009

129108

INFORMATION FOR PATIENTS SECTION

MetroGel-Vaginal®
(metronidazole vaginal gel)
0.75% Vaginal Gel

DIRECTIONS FOR USE

1. Filling the applicator

- Remove cap and puncture metal seal on tube with the pointed tip of cap. (See Figure 1)
- Screw end of applicator onto tube. (See Figure 2)
- Gently squeeze the tube from the bottom to fill applicator. Plunger will stop when the applicator is full. (See Figure 3)
- Unscrew applicator and replace cap on tube.

2. Inserting the applicator

- The applicator may be inserted while lying on your back with your knees bent or in any comfortable position.
- Hold filled applicator by barrel, and gently insert into vagina as far as it will comfortably go. (See Figure 4)
- Slowly press the plunger until it stops to deposit gel into vagina and then withdraw the applicator.

3. Care of the applicator

If physician prescribes twice-a-day dosing:

- After use, pull the plunger out of the barrel. (See Figure 5)
- Wash both plunger and barrel in warm soapy water and rinse thoroughly.
- To reassemble applicator, gently push plunger back into barrel.

IMPORTANT
For once-a-day dosing, apply one applicator full at bedtime. For twice-a-day dosing, apply one applicator full each morning and evening for five days, or as directed by physician.

WARNINGS

- If significant irritation develops from the use of this medication, discontinue use and consult your physician.
- Do not use during pregnancy except under the supervision of a physician.
- Keep this and all medications out of reach of children.
- For vaginal use only. Not for use in the eyes, on the skin or in the mouth.

Store at room temperature. Avoid exposure to extreme heat or cold.
See end of carton and bottom of tube for lot number and expiration date.

US patent #s 4,837,378; 5,536,743
Other patents pending

Manufactured for:
Graceway Pharmaceuticals, LLC
Bristol, TN 37620
By:
DPT Laboratories, Inc.
San Antonio, TX 78215

PRINCIPAL DISPLAY PANEL

MetroGel-Vaginal®(metronidazole vaginal gel)
0.75% Vaginal Gel
with 5 applicators
FOR INTRAVAGINAL USE ONLY. (NOT FOR OPHTHALMIC, DERMAL, OR ORAL USE.)
Rx Only
Net Wt. 70g

NDC 54868-3110-0